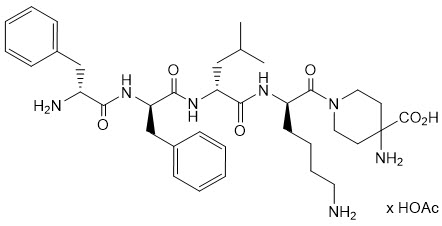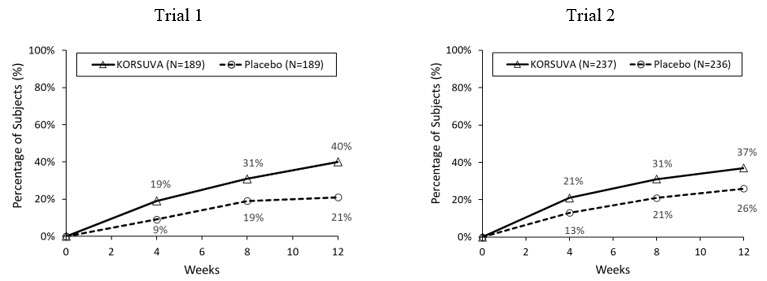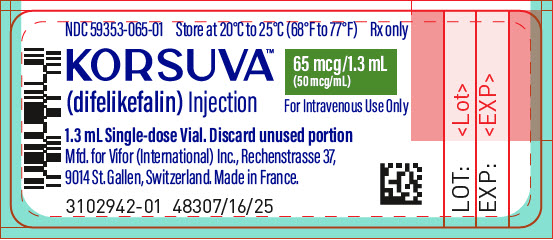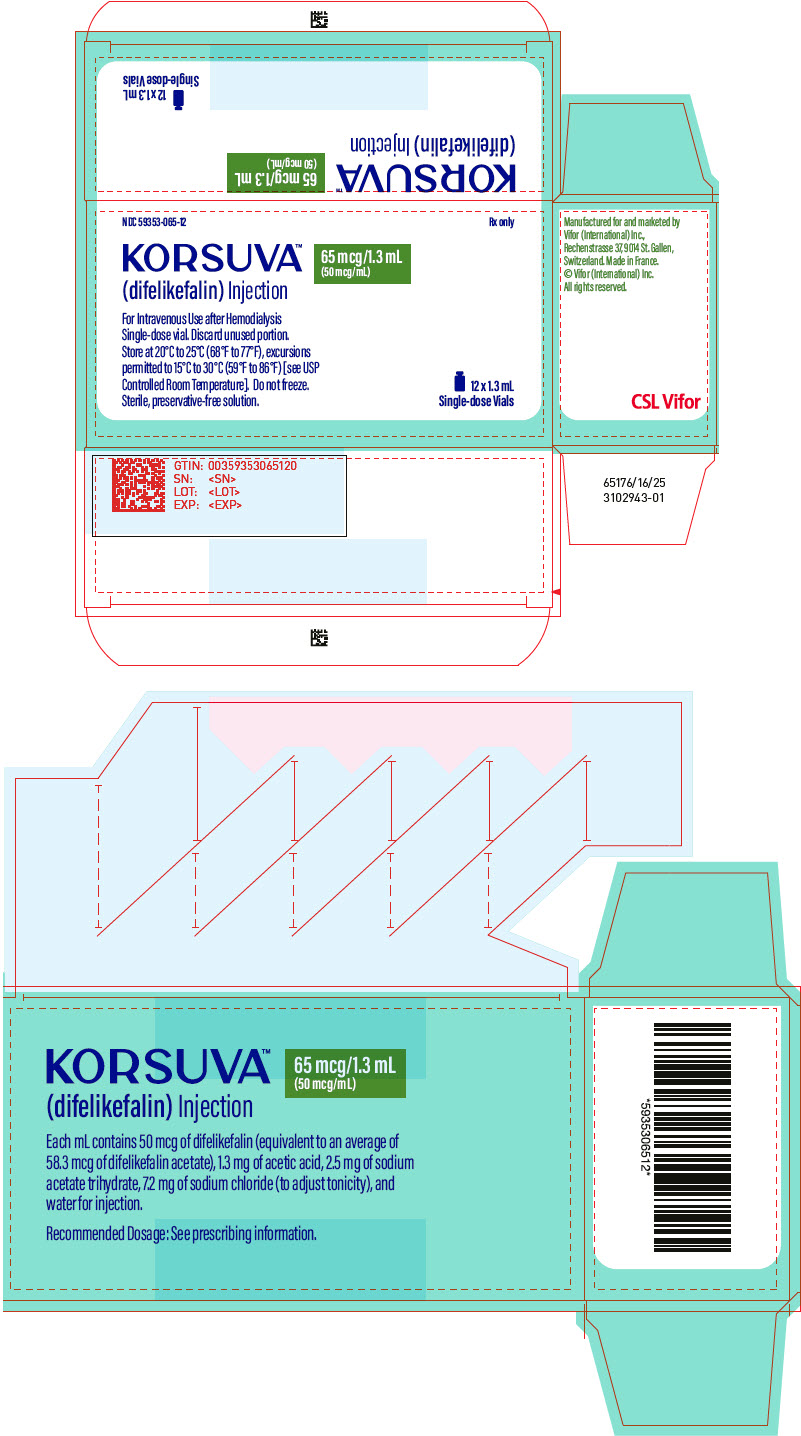 DRUG LABEL: Korsuva
NDC: 59353-065 | Form: INJECTION, SOLUTION
Manufacturer: Vifor (International), Inc.
Category: prescription | Type: HUMAN PRESCRIPTION DRUG LABEL
Date: 20250826

ACTIVE INGREDIENTS: DIFELIKEFALIN ACETATE 50 ug/1 mL

HIGHLIGHTS OF PRESCRIBING INFORMATION

These highlights do not include all the information needed to use KORSUVA safely and effectively. See full prescribing information for KORSUVA.
KORSUVA® (difelikefalin) injection, for intravenous use
Initial U.S. Approval: 2021

1 INDICATIONS AND USAGE

KORSUVA is a kappa opioid receptor agonist indicated for the treatment of moderate-to-severe pruritus associated with chronic kidney disease (CKD-aP) in adults undergoing hemodialysis (HD). (1)

Limitation of Use

Korsuva has not been studied in patients on peritoneal dialysis and is not recommended for use in this population. (1)

2 DOSAGE AND ADMINISTRATION

- Recommended dosage is 0.5 mcg/kg. (2.1)
- Administer by intravenous bolus injection into the venous line of the dialysis circuit at the end of each HD treatment. (2.1)
- Do not mix or dilute KORSUVA prior to administration. (2.2)
- Administer within 4 hours of syringe preparation. (2.3)
- See full prescribing information for additional recommendations on preparation and administration of KORSUVA. (2.2, 2.3)

3 DOSAGE FORMS AND STRENGTHS

Injection: 65 mcg /1.3 mL (50 mcg/mL) of difelikefalin (3)

4 CONTRAINDICATIONS

None

5 WARNINGS AND PRECAUTIONS

- Dizziness, Somnolence, Mental Status Changes, and Gait Disturbances: Dizziness, somnolence, mental status changes, and gait disturbances, including falls, have occurred. Centrally-acting depressant medications, sedating antihistamines, and opioid analgesics should be used with caution during treatment with KORSUVA. (5.1)
- Risk of Driving and Operating Machinery: May impair mental or physical abilities. Advise patients not to drive or operate dangerous machinery until the effect of KORSUVA on a patient's ability to drive or operate machinery is known. (5.2)

6 ADVERSE REACTIONS

The most common adverse reactions (incidence ≥2% and ≥1% higher than placebo) were diarrhea, dizziness, nausea, gait disturbances, including falls, hyperkalemia, headache, somnolence, and mental status change. (6)

To report SUSPECTED ADVERSE REACTIONS, contact Vifor (International) Inc. at 1-844-835-8277 or FDA at 1-800-FDA-1088 or www.fda.gov/medwatch.

8 USE IN SPECIFIC POPULATIONS

Severe Hepatic Impairment: Not recommended in patients with severe hepatic impairment. (8.6)

FULL PRESCRIBING INFORMATION

1 INDICATIONS AND USAGE

KORSUVA is indicated for the treatment of moderate-to-severe pruritus associated with chronic kidney disease (CKD-aP) in adults undergoing hemodialysis (HD).

Limitations of Use

KORSUVA has not been studied in patients on peritoneal dialysis and is not recommended for use in this population.

2 DOSAGE AND ADMINISTRATION

2.1 Dosage

- The recommended dosage of KORSUVA is 0.5 mcg/kg administered by intravenous bolus injection into the venous line of the dialysis circuit at the end of each HD treatment [see Dosage and Administration (2.3)].
- If a regularly scheduled HD treatment is missed, resume KORSUVA at the end of the next HD treatment.

2.2 Preparation Instructions

- Do not mix or dilute KORSUVA prior to administration.
- Inspect KORSUVA for particulate matter and discoloration prior to administration. The solution should be clear and colorless. Do not use KORSUVA vials if particulate matter or discoloration is observed.
- KORSUVA is supplied in a single-dose vial. Discard any unused product.
- Injection volume to be administered is determined by patient's target dry body weight in kilograms (one patient may use less than the full contents of the vial or use more than one vial). See Table 1.

Table 1. KORSUVA Injection Volumes Based on Target Dry Body Weight
Target Dry Body Weight Range (kg) | Injection Volume (mL) [Total Injection Volume (mL) = Patient Target Dry Body Weight (kg) x 0.01, rounded to the nearest tenth (0.1 mL). For patient target dry body weight outside of the ranges in Table 1, use this formula.]
36 – 44 | 0.4
45 – 54 | 0.5
55 – 64 | 0.6
65 – 74 | 0.7
75 – 84 | 0.8
85 – 94 | 0.9
95 – 104 | 1
105 – 114 | 1.1
115 – 124 | 1.2
125 – 134 | 1.3
135 – 144 | 1.4
145 – 154 | 1.5
155 – 164 | 1.6
165 – 174 | 1.7
175 – 184 | 1.8
185 – 194 | 1.9
195 – 204 | 2

2.3 Administration Instructions

- KORSUVA is removed by the dialyzer membrane and must be administered after blood is no longer circulating through the dialyzer.
- Administer KORSUVA by intravenous bolus injection into the venous line of the dialysis circuit at the end of each HD session.
  - The dose may be given either during or after rinse back of the dialysis circuit.
  - If the dose is given after rinse back, administer KORSUVA into the venous line followed by at least 10 mL of normal saline flush.
  - If the dose is given during rinse back, no additional normal saline is needed to flush the line.
- The dose must be administered within 4 hours of the syringe preparation. Discard any unused product.

3 DOSAGE FORMS AND STRENGTHS

Injection: 65 mcg/1.3 mL (50 mcg/mL) of difelikefalin as a clear, colorless solution in a single-dose glass vial.

4 CONTRAINDICATIONS

None

5 WARNINGS AND PRECAUTIONS

5.1 Dizziness, Somnolence, Mental Status Changes, and Gait Disturbances

Dizziness, somnolence, mental status changes, and gait disturbances, including falls, have occurred in patients taking KORSUVA and may subside over time with continued treatment [see Adverse Reactions (6.1)]. In Trial 1 and Trial 2, 17.0% of patients randomized to receive KORSUVA reported at least one of these adverse reactions, compared to 12.0% of patients who received placebo. The incidence of somnolence was higher in KORSUVA-treated subjects 65 years of age and older (7.0%) than in KORSUVA-treated subjects less than 65 years of age (2.8%). Concomitant use of centrally-acting depressant medications, sedating antihistamines and opioid analgesics may increase the likelihood of these adverse reactions and should be used with caution during treatment with KORSUVA.

5.2 Risk of Driving and Operating Machinery

Dizziness, somnolence, and mental status changes have occurred in patients taking KORSUVA. KORSUVA may impair the mental or physical abilities needed to perform potentially hazardous activities such as driving a car and operating machinery. Advise patients not to drive or operate dangerous machinery until the effect of KORSUVA on a patient's ability to drive or operate machinery is known.

6 ADVERSE REACTIONS

The following clinically significant adverse reactions are described elsewhere in the labeling:

- Dizziness, Somnolence, Mental Status Changes, and Gait Disturbances [see Warnings and Precautions (5.1)]

6.1 Clinical Trials Experience

Because clinical trials are conducted under widely varying conditions, adverse reaction rates observed in the clinical trials of a drug cannot be directly compared to rates in the clinical trials of another drug and may not reflect the rates observed in practice.

A total of 1306 subjects undergoing HD who had moderate-to-severe pruritus were treated with KORSUVA in placebo-controlled and uncontrolled Phase 3 clinical trials. Of these, 711 were treated for at least 6 months and 400 were treated for at least one year.

Two placebo-controlled Phase 3 trials (Trial 1 and Trial 2), in subjects undergoing HD who had moderate-to-severe pruritus were pooled to evaluate the safety of KORSUVA in comparison to placebo up to 12 weeks. In total, 848 subjects were evaluated (424 in KORSUVA group and 424 in placebo group). The mean age of the subjects was 59 years (range 22 to 88 years), and 59% of the subjects were male. Of the total subjects, 61% were White, 29% were Black or African American, and 5% were Asian.

Table 2 summarizes the adverse reactions that occurred at a rate of ≥2% in the KORSUVA group and ≥1% higher than that of the placebo group during the 12-week placebo-controlled period of Trials 1 and 2. The percentage of subjects who discontinued treatment due to any adverse reaction was 2.6% for subjects taking KORSUVA and 0.7% for subjects taking placebo. The most common adverse reactions (≥0.5% of subjects) leading to discontinuation were dizziness (0.9% for KORSUVA and 0.2% for placebo), mental status change (0.7% and 0.2%, respectively), nausea (0.5% and 0%, respectively), and headache (0.5% and 0%, respectively). The percentage of subjects who developed serious adverse reactions was 4.5% in the KORSUVA group and 2.8% in the placebo group.

Table 2: Adverse Reactions in ≥ 2% of KORSUVA-Treated Subjects with Moderate-to-Severe CKD-aP Undergoing HD and ≥ 1% Higher Than Placebo in Trials 1 and 2
Adverse Reactions | Placebo (N=424) n (%) | KORSUVA (N=424) n (%)
Diarrhea | 24 (5.7) | 38 (9.0)
Dizziness | 16 (3.8) | 29 (6.8)
Nausea | 19 (4.5) | 28 (6.6)
Gait Disturbances [Gait disturbances includes: preferred terms of falls and gait disturbances] | 23 (5.4) | 28 (6.6)
Hyperkalemia | 15 (3.5) | 20 (4.7)
Headache | 11 (2.6) | 19 (4.5)
Somnolence | 10 (2.4) | 18 (4.2)
Mental Status Change [Mental Status Change includes: preferred terms of confusional state and mental status change.] | 6 (1.4) | 14 (3.3)

Description of Selected Adverse Reactions

Gait Disturbances, including Falls

Gait disturbances, including falls, were reported in 6.6% of subjects receiving KORSUVA compared to 5.4% of subjects who received placebo. Falls were reported as serious adverse reactions in < 1% of subjects receiving KORSUVA and placebo, with one subject discontinuing KORSUVA due to gait disturbance.

Dizziness

Dizziness was reported in 6.8% of subjects randomized to KORSUVA compared to 3.8% of subjects who received placebo. Dizziness occurred within the first 3 weeks of treatment and was generally transient. Dizziness was serious in 0.2% of KORSUVA-treated subjects compared to 0% of subjects who received placebo and led to discontinuation in 0.9% of KORSUVA-treated subjects compared to 0.2% of subjects who received placebo.

Somnolence

Somnolence was reported in 4.2% of subjects randomized to receive KORSUVA compared to 2.4% of subjects who received placebo. Somnolence occurred within the first 3 weeks of treatment and tended to subside with continued dosing. Somnolence was serious in 0.2% of KORSUVA-treated subjects compared to 0% of subjects who received placebo. There were no subjects who discontinued KORSUVA due to an adverse reaction of somnolence.

Mental Status Change

Mental status change (including confusional state) was reported in 3.3% of subjects randomized to receive KORSUVA compared to 1.4% of subjects who received placebo. Most events tended to subside with continued dosing. Mental status change adverse reactions were serious in 1.4% of KORSUVA-treated subjects compared to 0.5% of subjects who received placebo and led to discontinuation in 0.7% of KORSUVA-treated subjects compared to 0.2% of subjects who received placebo.

Hyperkalemia

Hyperkalemia was found in 4.7% of subjects who received KORSUVA compared to 3.5% of subjects who received placebo. The incidence of hyperkalemia was higher in subjects who took concomitant opioids regardless of treatment and was almost doubled in the KORSUVA group (11.7%) compared to the placebo group (6.2%). The clinical relevance of this is unknown.

8 USE IN SPECIFIC POPULATIONS

8.1 Pregnancy

Risk Summary

The limited human data on use of KORSUVA in pregnant women are not sufficient to evaluate a drug-associated risk for major birth defects or miscarriage. In animal reproduction studies, intravenous injection of difelikefalin to pregnant rats and rabbits during the period of organogenesis at doses 711 and 10 times the maximum recommended human dose (MRHD), respectively, resulted in no adverse effects in either rats or rabbits (see Data).

The estimated background risk of major birth defects and miscarriage for the indicated population is unknown. In the U.S. general population, the estimated background risk of major birth defects and miscarriage in clinically recognized pregnancies is 2-4% and 15-20%, respectively.

Data

Animal Data

In an embryofetal development study, difelikefalin was administered by intravenous injection to pregnant rats at doses of 0.25, 2.5, and 25 mg/kg/day during the period of organogenesis. Difelikefalin was not associated with embryofetal lethality or fetal malformations. Difelikefalin increased the incidences of skeletal variations (wavy ribs and incompletely ossified ribs) at the dose of 25 mg/kg/day (711 times the MRHD based on AUC comparison).

In an embryofetal development study, difelikefalin was administered by intravenous injection to pregnant rabbits at doses of 0.025, 0.05, and 0.1 mg/kg/day during the period of organogenesis. Maternal toxicity evidenced by decreased maternal body weight gain was noted in all dose groups. Difelikefalin was not associated with embryofetal lethality or fetal malformations at doses up to 0.1 mg/kg/day (10 times the MRHD based on AUC comparison).

In a prenatal and postnatal development study, difelikefalin was administered by intravenous injection to pregnant rats at doses of 0.6, 2.5, and 10 mg/kg/day beginning on gestation day 7 and continuing through lactation day 20. Persisting effects on decreased maternal body weight and/or maternal body weight gain as well as food consumption were noted at doses greater than or equal to 2.5 mg/kg/day (68 times the MRHD based on AUC comparison). No maternal effects were observed at 0.6 mg/kg/day (14 times the MRHD based on AUC comparison). No difelikefalin-related effects on postnatal developmental, neurobehavioral, or reproductive performance of offspring were noted at doses up to 10 mg/kg/day (282 times the MRHD based on AUC comparison).

8.2 Lactation

Risk Summary

There are no data regarding the presence of KORSUVA in human milk or effects on the breastfed infant or on milk production.

Studies in rats showed difelikefalin was transferred into the milk in lactating rats. When a drug is present in animal milk, it is likely that the drug will be present in human milk. The developmental and health benefits of breastfeeding should be considered along with the mother's clinical need for KORSUVA and any potential adverse effects on the breastfed child from KORSUVA or from the underlying maternal condition.

Data

Animal Data

Difelikefalin was administered to lactating rats by intravenous injection at doses of 0.6, 2.5, or 10 mg/kg/day from gestation day 7 through lactation day 14. Difelikefalin was detected in the milk of the lactating rats with the concentration ratio for milk:plasma of 0.04 to 0.05 across the doses. There was no measurable difelikefalin in the plasma of nursing pups.

8.4 Pediatric Use

The safety and effectiveness of KORSUVA in pediatric patients have not been established.

8.5 Geriatric Use

Of the 848 subjects in the placebo-controlled studies who received KORSUVA, 278 subjects (32.8%) were 65 years of age and older and 98 subjects (11.6%) were 75 years of age and older. No overall differences in safety or effectiveness of KORSUVA have been observed between patients 65 years of age and older and younger adult subjects, with the exception of the incidence of somnolence which was higher in KORSUVA-treated subjects 65 years of age and older (7.0%) than in KORSUVA-treated subjects less than 65 years of age (2.8%), and was comparable in both placebo age groups (3.0% and 2.1%, respectively). No differences in plasma concentrations of KORSUVA were observed between subjects 65 years of age and older and younger adult subjects [see Clinical Pharmacology (12.3)].

8.6 Hepatic Impairment

The influence of mild-to-moderate hepatic impairment on the pharmacokinetics of KORSUVA was evaluated in a population pharmacokinetic analysis which concluded that no KORSUVA dosage adjustments are needed in these populations [see Clinical Pharmacology (12.3)]. The influence of severe hepatic impairment on the pharmacokinetics of KORSUVA in subjects undergoing HD has not been evaluated; therefore, use of KORSUVA in this population is not recommended.

10 OVERDOSAGE

Single doses of KORSUVA up to 12 times and multiple doses of KORSUVA up to 5 times the recommended dosage of 0.5 mcg/kg were administered in clinical studies in subjects undergoing HD. A dose-dependent increase in adverse reactions, including dizziness, somnolence, mental status changes, paresthesia, fatigue, hypertension, and vomiting, were observed.

In the event of overdosage, provide the appropriate medical attention based on patient's clinical status. Difelikefalin is primarily eliminated by the kidneys with a low plasma protein binding of approximately 23% to 28% in dialysis patients. Hemodialysis for 4 hours using a high-flux dialyzer effectively cleared approximately 70% to 80% of difelikefalin from plasma, and difelikefalin was not detectable in plasma at the end of the second of two dialysis cycles. [see Clinical Pharmacology (12.3)].

11 DESCRIPTION

KORSUVA (difelikefalin) is a kappa opioid receptor agonist. Difelikefalin is a synthetic peptide with a single stereoisomer and is present as an acetate salt. Difelikefalin acetate is a white to off-white powder with a molecular formula of C36H53N7O6∙xAcOH (1.0≤ × ≤2.0) and a molecular weight of 679.4 g/mol (mono- isotopic; free base). It is soluble in water. The chemical name of difelikefalin acetate is 4-amino-1-(D-phenylalanyl-D-phenylalanyl-D-leucyl-D-lysyl)piperidine-4-carboxylic acid, acetate salt.

The chemical structure is:

KORSUVA (difelikefalin) injection is supplied in a single-dose vial containing 65 mcg/1.3 mL (50 mcg/mL) of difelikefalin as a sterile, preservative-free, clear and colorless solution for intravenous injection.

KORSUVA is formulated as an isotonic 40 mM acetate buffer solution with an osmolality of 250 to 350 mOsm and a pH of 4.5.

Each milliliter of KORSUVA injection contains 50 mcg of difelikefalin (equivalent to an average of 58.3 mcg of difelikefalin acetate), 1.3 mg of acetic acid, 2.5 mg of sodium acetate trihydrate, 7.2 mg of sodium chloride (to adjust tonicity), and water for injection.

12 CLINICAL PHARMACOLOGY

12.1 Mechanism of Action

KORSUVA is a kappa opioid receptor (KOR) agonist. The relevance of KOR activation to therapeutic effectiveness is not known.

12.2 Pharmacodynamics

Difelikefalin exposure-response relationships and the time course of pharmacodynamic response are unknown.

Cardiac Electrophysiology

At a dose 6 times the recommended dosage, difelikefalin does not prolong the QTc interval to any clinically relevant extent.

12.3 Pharmacokinetics

The pharmacokinetics of difelikefalin is dose proportional over a single dosage range from 1 to 3 mcg/kg (2 to 6 times the recommended dosage) and multiple intravenous dosage range from 0.5 to 2.5 mcg/kg (1 to 5 times the recommended dosage) in chronic kidney disease patients undergoing HD. Steady-state was reached after the second administered dosage and the mean accumulation ratio was up to 1.6.

Distribution

The mean volume of distribution of difelikefalin is approximately 238 mL/kg. Difelikefalin binding to human plasma protein in dialysis patients is 23% to 28%.

Elimination

The half-life of difelikefalin in HD subjects prior to dialysis ranged between 23 and 31 hours. Following administration of radiolabeled difelikefalin, >99% of circulating radioactivity was present in plasma as parent. Hemodialysis reduced the difelikefalin plasma concentrations by 70% to 80% and difelikefalin was not detectable in plasma after 2 dialysis cycles.

Metabolism

Difelikefalin is not metabolized by cytochrome P450 (CYP) enzymes CYP1A2, CYP2C19, CYP2C8, CYP2C9, CYP2D6 or CYP3A observed in human hepatic microsomes or hepatocytes, in vitro.

Excretion

Following administration of difelikefalin to HD patients, 11% of the dosage was excreted in urine, 59% in feces, and 20% in dialysate fluid.

Specific Populations

No clinically significant differences in the pharmacokinetics of difelikefalin were observed based on age (25 to 80 years of age), sex, race/ethnicity, or mild-to-moderate hepatic impairment. The effect of severe hepatic impairment on the pharmacokinetics of difelikefalin is unknown [see Use in Specific Populations (8.6)].

Drug Interaction Studies

Clinical Studies

No clinical studies evaluating the drug interaction potential of difelikefalin were conducted.

In Vitro Studies

Cytochrome P450 (CYP) Enzymes: Difelikefalin did not inhibit CYP enzymes (CYP1A2, CYP2B6, CYP2C8, CYP2C9, CYP2C19, CYP3A, or CYP2D6), or induce CYP enzymes (CYP1A2, CYP2B6, or CYP3A) and is not a substrate of CYP450 enzymes (CYP1A2, CYP2C19, CYP2C8, CYP2C9, CYP2D6 or CYP3A).

Uridine diphosphate (UDP)-glucuronosyl transferase (UGT) Enzymes: Difelikefalin is not an inhibitor of UGT1A3, UGT1A9, or UGT2B7.

Transporter Systems: Difelikefalin did not inhibit BCRP, Pgp, OAT1, OAT3, OCT1, OCT2, OATP1B1, OATP1B3, MATE1, or, MATE2-K human transporters and is not a substrate of OAT1, OAT2, OAT3, OATP1A2, OCT2, OCT3, LAT1, PEPT1, PEPT2, ASBT, BSEP, MRP2, OATP1B1, OATP1B3, OATP2B1, OCT1, OCTN1, OCTN2, Pgp, BCRP, OSTα/β, MATE1, or, MATE2-K.

13 NONCLINICAL TOXICOLOGY

13.1 Carcinogenesis, Mutagenesis, Impairment of Fertility

In a 2-year carcinogenicity study in rats, difelikefalin was not carcinogenic when administered via subcutaneous injection at doses up to 1.0 mg/kg/day (597 times the MRHD based on AUC comparison). Difelikefalin was not carcinogenic in a 6-month carcinogenicity study in transgenic rasH2 mice at subcutaneous doses up to 30 mg/kg/day.

Difelikefalin was negative for genotoxicity in a bacterial reverse mutation assay, an in vitro mammalian chromosomal aberration assay, and an in vivo mouse micronucleus assay.

Difelikefalin administered via intravenous injection caused a significant decrease in the number of estrous cycles per 14 days (i.e., prolonged diestrus) in female rats at doses greater than or equal to 2.5 mg/kg/day (56 times the MRHD based on AUC comparison). Difelikefalin had no effects on mating index, fertility index, or any ovarian or uterine parameters in female rats at doses up to 25 mg/kg/day (635 times the MRHD based on AUC comparison). Difelikefalin did not impair male fertility at doses up to 25 mg/kg/day (971 times the MRHD based on AUC comparison).

14 CLINICAL STUDIES

The efficacy of KORSUVA was evaluated in two randomized, multicenter, double-blind, placebo-controlled trials (Trial 1 [NCT03422653] and Trial 2 [NCT03636269]) that enrolled a total of 851 subjects 18 years of age and older undergoing HD who had moderate-to-severe pruritus. In both trials, subjects received intravenous bolus injections of KORSUVA 0.5 mcg per kilogram of dry body weight into the venous line of the hemodialysis circuit at the end of each hemodialysis session or placebo three times per week for 12 weeks. In both trials, a 7-day run-in period prior to randomization was used to confirm that each subject had moderate-to-severe pruritus and to establish a baseline itch intensity, as measured by the patient-reported daily 24-hour Worst Itching Intensity Numerical Rating Scale (WI-NRS) scores (0 "no itch" to 10 "worst itch imaginable").

The mean (SD) baseline WI-NRS score was 7.1 (1.5) in Trial 1 and 7.2 (1.4) in Trial 2. At baseline in Trial 1, 61% of subjects were male, 49% were White, 42% were Black or African American, the mean age was 57 years (range 22 to 88 years), and 40% of subjects were using prior anti-pruritic medications (including sedating antihistamines) and continued the use throughout the trial. At baseline in Trial 2, 58% of subjects were male, 70% were White, 19% were Black or African American, the mean age was 60 years (range 23 to 90 years), and 36% of subjects were using prior anti-pruritic medications (including sedating antihistamines) and continued the use throughout the trial.

In each trial, efficacy was assessed based on the proportion of subjects achieving a 4-point or greater improvement (reduction) from baseline in the weekly mean of the daily 24-hour WI-NRS score at Week 12.

The results of the KORSUVA trials (Trials 1 and 2) are presented in Table 3 and Figure 1.

Table 3. Efficacy Results of Subjects with Moderate-to-Severe CKD-aP Undergoing HD at Week 12 (Trials 1 & 2)
 | Trial 1 |  | Trial 2
 | KORSUVA 0.5 mcg/kg 3 times weekly N=189 | Placebo N=189 | KORSUVA 0.5 mcg/kg 3 times weekly N=237 | Placebo N=236
Percentage of subjects with ≥4-point improvement from baseline in WI-NRS score | 40% | 21% | 37% | 26%
Difference from Placebo (95% CI) | 19% (9%, 28%) |  | 12% (3%, 20%)

Figure 1: Percentage of Subjects with Moderate-to-Severe CKD-aP Undergoing HD with a ≥4-point Improvement from Baseline on the WI-NRS in Trial 1 and Trial 2

Itch reduction was seen by Week 4 and sustained through Week 12.

16 HOW SUPPLIED/STORAGE AND HANDLING

How Supplied

KORSUVA (difelikefalin) injection is supplied as a sterile, clear and colorless solution in 1.3 mL single-dose, glass vials:

NDC 59353-065-01: 65 mcg/1.3 mL (50 mcg/mL) single-dose vial

NDC 59353-065-12: Carton containing 12 vials

Storage and Handling

Store vials at 20°C to 25°C (68°F to 77°F), excursions permitted to 15°C to 30°C (59°F to 86°F) [see USP Controlled Room Temperature]. Do not freeze.

KORSUVA injection must be administered within 4 hours of syringe preparation; prepared syringes can be stored at ambient temperature 20°C to 25°C (68°F to 77°F) until dosing [see Dosage and Administration (2.2, 2.3)] .

KORSUVA injection is supplied in a single-dose vial. Any unused drug remaining after injection must be discarded.

17 PATIENT COUNSELING INFORMATION

Dizziness, Somnolence, Mental Status Changes, and Gait Disturbances

Inform patients that dizziness, somnolence, mental status changes, and gait disturbances, including falls, can occur during treatment with KORSUVA [see Adverse Reactions (6.1)]. Somnolence is more likely to happen to patients who are age 65 years or older.

Inform patients that concomitant treatment with centrally-acting depressants, sedating antihistamines and opioid analgesics may increase the likelihood of these adverse reactions and these medications should be used with caution during treatment with KORSUVA [see Warnings and Precautions (5.1)].

Driving or Operating Machinery

Inform patients that KORSUVA may impair the ability to perform potentially hazardous activities such as driving a car or operating heavy machinery. Advise patients not to drive or operate machinery until they know how they will react to KORSUVA [see Warnings and Precautions (5.2)].

Manufactured for and marketed by
Vifor (International) Inc.,
Rechenstrasse 37, 9014 St. Gallen, Switzerland

PRINCIPAL DISPLAY PANEL - 1.3 mL Vial Label

NDC 59353-065-01
Store at 20°C to 25°C (68°F to 77°F)
Rx only

KORSUVA™
(difelikefalin) Injection

65 mcg/1.3 mL
(50 mcg/mL)

For Intravenous Use Only

1.3 mL Single-dose Vial. Discard unused portion
Mfd. for Vifor (International) Inc., Rechenstrasse 37,
9014 St. Gallen, Switzerland. Made in France.

3102942-01 48307/16/25

PRINCIPAL DISPLAY PANEL - 1.3 mL Tray Carton

NDC 59353-065-12
Rx only

KORSUVA™
(difelikefalin) Injection

65 mcg/1.3 mL
(50 mcg/mL)

For Intravenous Use after Hemodialysis
Single-dose vial. Discard unused portion.
Store at 20°C to 25°C (68°F to 77°F), excursions
permitted to 15°C to 30°C (59°F to 86°F) [see USP
Controlled Room Temperature]. Do not freeze.
Sterile, preservative-free solution.

12 x 1.3 mL
Single-dose Vials